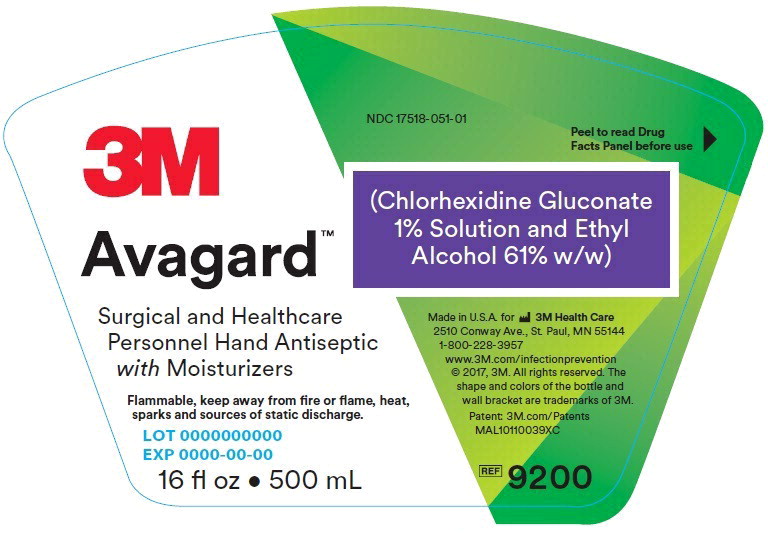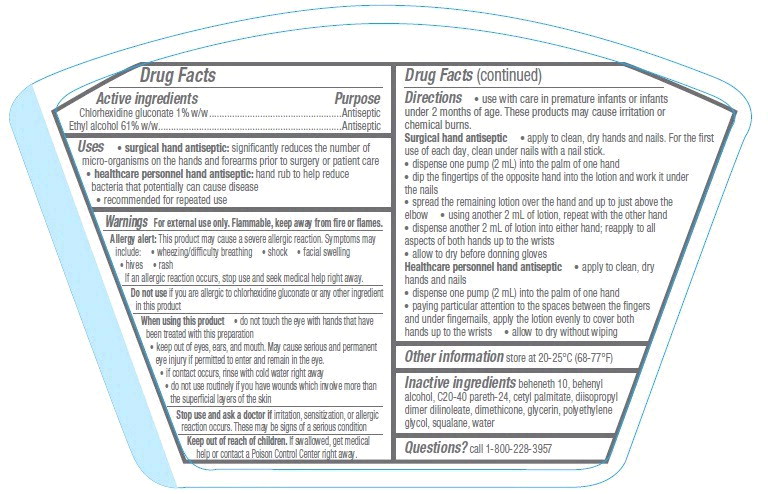 DRUG LABEL: 3M Avagard
NDC: 17518-051 | Form: LOTION
Manufacturer: Solventum US LLC
Category: otc | Type: HUMAN OTC DRUG LABEL
Date: 20240801

ACTIVE INGREDIENTS: Chlorhexidine Gluconate 8.3 mg/1 mL; Alcohol 506.3 mg/1 mL
INACTIVE INGREDIENTS: Beheneth-10; Docosanol; Cetyl Palmitate; Dimethicone; Glycerin; polyethylene glycol, unspecified; Squalane; Water

Drug Facts

Active ingredients

Chlorhexidine gluconate 1% w/w

Ethyl alcohol 61% w/w

Purpose

Antiseptic

Antiseptic

Uses

- surgical hand antiseptic: significantly reduces the number of micro-organisms on the hands and forearms prior to surgery or patient care
- healthcare personnel hand antiseptic: hand rub to help reduce bacteria that potentially can cause disease
- recommended for repeated use

Warnings

For external use only. Flammable, keep away from fire or flames.

Allergy alert: This product may cause a severe allergic reaction. Symptoms may include:

- wheezing/difficulty breathing
- shock
- facial swelling
- hives
- rash

If an allergic reaction occurs, stop use and seek medical help right away.

Do not use if you are allergic to chlorhexidine gluconate or any other ingredient in this product

When using this product

- do not touch the eye with hands that have been treated with this preparation
- keep out of eyes, ears, and mouth. May cause serious and permanent eye injury if permitted to enter and remain in the eye.
- if contact occurs, rinse with cold water right away
- do not use routinely if you have wounds which involve more than the superficial layers of the skin

Stop use and ask a doctor if irritation, sensitization, or allergic reaction occurs. These may be signs of a serious condition

Keep out of reach of children. If swallowed, get medical help or contact a Poison Control Center right away.

Directions

- use with care in premature infants or infants under 2 months of age. These products may cause irritation or chemical burns.

Surgical hand antiseptic

- apply to clean, dry hands and nails. For the first use of each day, clean under nails with a nail stick.
- dispense one pump (2 mL) into the palm of one hand
- dip the fingertips of the opposite hand into the lotion and work it under the nails
- spread the remaining lotion over the hand and up to just above the elbow
- using another 2 mL of lotion, repeat with the other hand
- dispense another 2 mL of lotion into either hand; reapply to all aspects of both hands up to the wrists
- allow to dry before donning gloves

Healthcare personnel hand antiseptic

- apply to clean, dry hands and nails
- dispense one pump (2 mL) into the palm of one hand
- paying particular attention to the spaces between the fingers and under fingernails, apply the lotion evenly to cover both hands up to the wrists
- allow to dry without wiping

Other information

store at 20-25°C (68-77°F)

Inactive ingredients

beheneth 10, behenyl alcohol, C20-40 pareth-24, cetyl palmitate, diisopropyl dimer dilinoleate, dimethicone, glycerin, polyethylene glycol, squalane, water

Questions?

Call 1-800-228-3957

Principle Display Panel – 500mL Bottle Label

3M

NDC 17518-051-01

Avagard™

(Chlorhexidine Gluconate 1% Solution and Ethyl Alcohol 61% w/w)

Surgical and Healthcare Personnel Hand Antiseptic with Moisturizers

Peel to read Drug Facts Panel before use

Made in U.S.A. for 3M Health Care

2510 Conway Ave., St. Paul, MN 55144

1-800-228-3957

www.3M.com/infectionprevention

© 2017, 3M. All rights reserved. The shape and colors of the bottle and wall bracket are trademarks of 3M.

Patent: 3M.com/Patents

MAL10110039XC

Flammable, keep away from fire or flame, heat, sparks and sources of static discharge.

LOT 0000000000

EXP 0000-00-00

16 fl oz • 500 mL

REF 9200